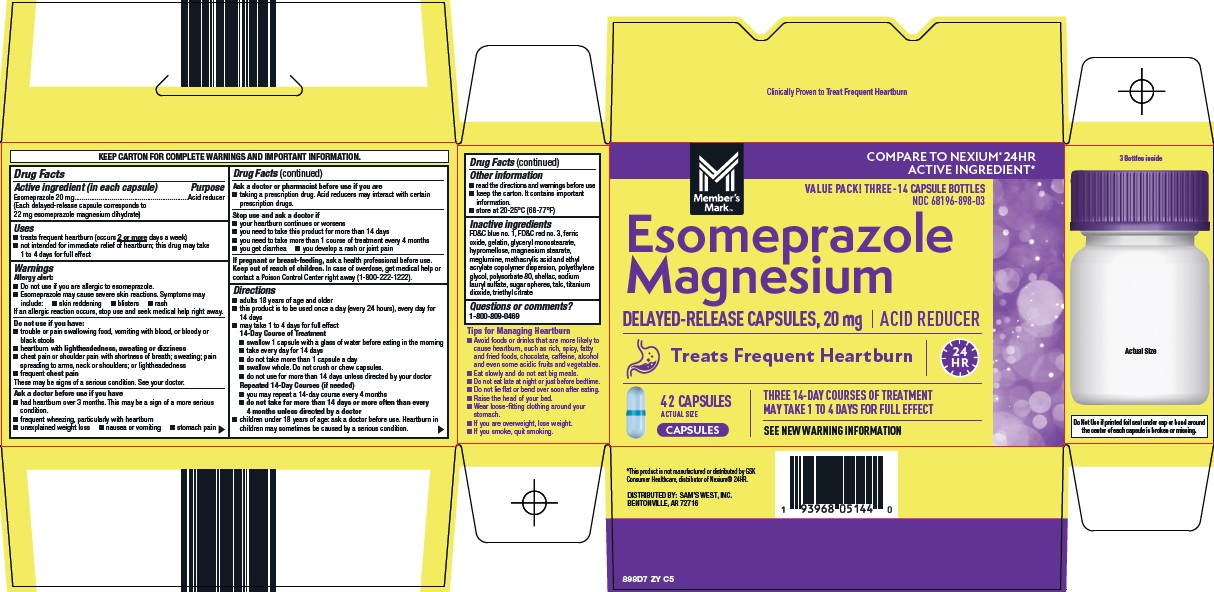 DRUG LABEL: members mark esomeprazole magnesium
NDC: 68196-898 | Form: CAPSULE, DELAYED RELEASE
Manufacturer: Sam's West Inc
Category: otc | Type: HUMAN OTC DRUG LABEL
Date: 20260207

ACTIVE INGREDIENTS: ESOMEPRAZOLE 20 mg/1 1
INACTIVE INGREDIENTS: FD&C BLUE NO. 1; FD&C RED NO. 3; FERRIC OXIDE RED; GELATIN, UNSPECIFIED; GLYCERYL MONOSTEARATE; HYPROMELLOSE, UNSPECIFIED; MAGNESIUM STEARATE; MEGLUMINE; METHACRYLIC ACID AND ETHYL ACRYLATE COPOLYMER; POLYETHYLENE GLYCOL, UNSPECIFIED; POLYSORBATE 80; SHELLAC; SODIUM LAURYL SULFATE; TALC; TITANIUM DIOXIDE; TRIETHYL CITRATE

Sam’s West, Inc. Esomeprazole Magnesium Drug Facts

Active ingredient (in each capsule)

Esomeprazole 20 mg

(Each delayed-release capsule corresponds to 22 mg esomeprazole magnesium dihydrate)

Purpose

Acid reducer

Uses

- treats frequent heartburn (occurs 2 or more days a week)
- not intended for immediate relief of heartburn; this drug may take 1 to 4 days for full effect

Warnings

Allergy alert:

- Do not use if you are allergic to esomeprazole.
- Esomeprazole may cause severe skin reactions. Symptoms may include:
  - skin reddening
  - blisters
  - rash

If an allergic reaction occurs, stop use and seek medical help right away.

Do not use if you have:

- trouble or pain swallowing food, vomiting with blood, or bloody or black stools
- heartburn with lightheadedness, sweating or dizziness
- chest pain or shoulder pain with shortness of breath; sweating; pain spreading to arms, neck or shoulders; or lightheadedness
- frequent chest pain

These may be signs of a serious condition. See your doctor.

Ask a doctor before use if you have

- had heartburn over 3 months. This may be a sign of a more serious condition.
- frequent wheezing, particularly with heartburn
- unexplained weight loss
- nausea or vomiting
- stomach pain

Ask a doctor or pharmacist before use if you are

- taking a prescription drug. Acid reducers may interact with certain prescription drugs.

Stop use and ask a doctor if

- your heartburn continues or worsens
- you need to take this product for more than 14 days
- you need to take more than 1 course of treatment every 4 months
- you get diarrhea
- you develop a rash or joint pain

If pregnant or breast-feeding,

ask a health professional before use.

Keep out of reach of children.

In case of overdose, get medical help or contact a Poison Control Center right away (1-800-222-1222).

Directions

- adults 18 years of age and older
- this product is to be used once a day (every 24 hours), every day for 14 days
- may take 1 to 4 days for full effect
14-Day Course of Treatment
- swallow 1 capsule with a glass of water before eating in the morning
- take every day for 14 days
- do not take more than 1 capsule a day
- swallow whole. Do not crush or chew capsules.
- do not use for more than 14 days unless directed by your doctor
Repeated 14-Day Courses (if needed)
- you may repeat a 14-day course every 4 months
- do not take for more than 14 days or more often than every 4 months unless directed by a doctor
- children under 18 years of age: ask a doctor before use. Heartburn in children may sometimes be caused by a serious condition.

Other information

- read the directions and warnings before use
- keep the carton. It contains important information.
- store at 20-25°C (68-77°F)

Inactive ingredients

FD&C blue no. 1, FD&C red no. 3, ferric oxide, gelatin, glyceryl monostearate, hypromellose, magnesium stearate, meglumine, methacrylic acid and ethyl acrylate copolymer dispersion, polyethylene glycol, polysorbate 80, shellac, sodium lauryl sulfate, sugar spheres, talc, titanium dioxide, triethyl citrate

Questions or comments?

1-800-809-0469

Package/Label Principal Display Panel

Member’s Mark™

COMPARE TO NEXIUM® 24HR ACTIVE INGREDIENT

VALUE PACK! THREE – 14 CAPSULE BOTTLES

Esomeprazole Magnesium

DELAYED-RELEASE CAPSULES, 20 mg | ACID REDUCER

Treats Frequent Heartburn | 24 HR

42 CAPSULES

ACTUAL SIZE

CAPSULES

THREE 14-DAY COURSES OF TREATMENT

MAY TAKE 1 TO 4 DAYS FOR FULL EFFECT

SEE NEW WARNING INFORMATION